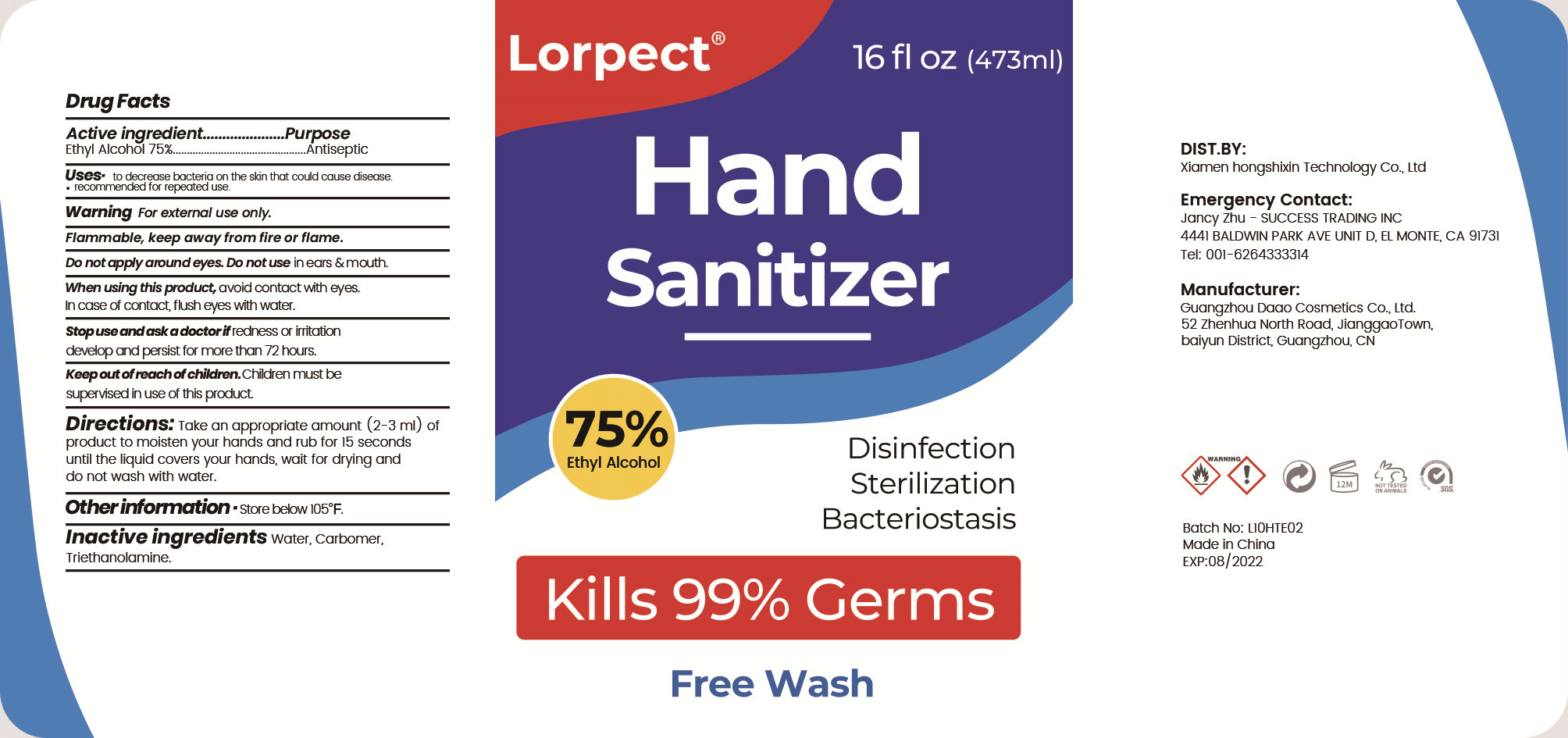 DRUG LABEL: Hand Sanitizer
NDC: 96175-002 | Form: GEL
Manufacturer: XIAMEN HONGSHIXIN TECHNOLOGY CO.,LTD
Category: otc | Type: HUMAN OTC DRUG LABEL
Date: 20200803

ACTIVE INGREDIENTS: ALCOHOL 354.75 mL/473 mL
INACTIVE INGREDIENTS: CARBOMER HOMOPOLYMER, UNSPECIFIED TYPE; TROLAMINE; WATER

DOSAGE AND ADMINISTRATION

store below 105°F.

INACTIVE INGREDIENT

WATER

CARBOMER

TRIETHANOLAMINE

INDICATIONS AND USAGE

Take an appropriate amount (2-3 ml) of product to moisten your hands and rub for 15 seconds until the liquid covers your hands, wait for drying and do not wash with water.

ACTIVE INGREDIENT

ALCOHOL

keep out of reach of children

PURPOSE

Disinfection
Sterilization
No Rinseing

WARNINGS

For external use only.Flammable, keep away from fire or flame.